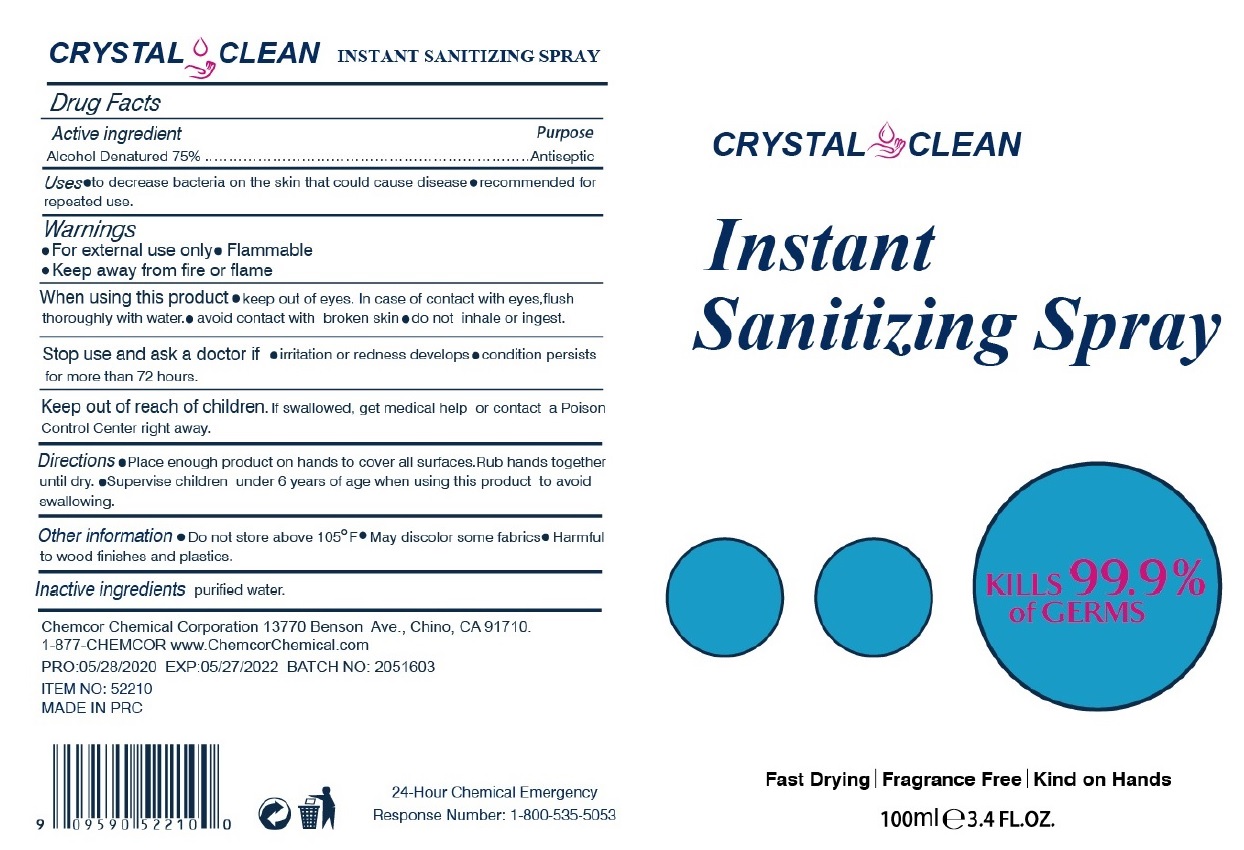 DRUG LABEL: Instant Sanitizing
NDC: 68041-003 | Form: SPRAY
Manufacturer: Chemcor Chemical Corporation
Category: otc | Type: HUMAN OTC DRUG LABEL
Date: 20230102

ACTIVE INGREDIENTS: ALCOHOL 75 mL/100 mL
INACTIVE INGREDIENTS: WATER

CRYSTAL CLEAN Instant Sanitizing Spray

Active ingredient

Alcohol Denatured 75%

Purpose

Antiseptic

INDICATIONS AND USAGE

Uses •to decrease bacteria on the skin that could cause disease •recommended for repeated use.

Warnings

•For external use only • Flammable

•Keep away from fire or flame

When using this product •keep out of eyes. In case of contact with eyes,flush thoroughly with water. •avoid contact with broken skin •do not inhale or ingest.

Stop use and ask a doctor if •irritation or redness develops •condition persists for more than 72 hours.

Keep out of reach of children. If swallowed, get medical help or contact a Poison Control Center right away.

DOSAGE AND ADMINISTRATION

Directions •Place enough product on hands to cover all surfaces.Rub hands together until dry. •Supervise children under 6 years of age when using this product to avoid swallowing.

Other information •Do not store above 105°F •May discolor some fabrics •Harmful to wood finishes and plastics.

Inactive ingredients purified water.

KILLS 99.9% of GERMS

Fast Drying | Fragrance Free | Kind on Hands

Chemcor Chemical Corporation 13770 Benson Ave., Chino, CA 91710.

1-877-CHEMCOR www.ChemcorChemical.com

MADE IN PRC

24-Hour Chemical Emergency

Response Number: 1-800-535-5053